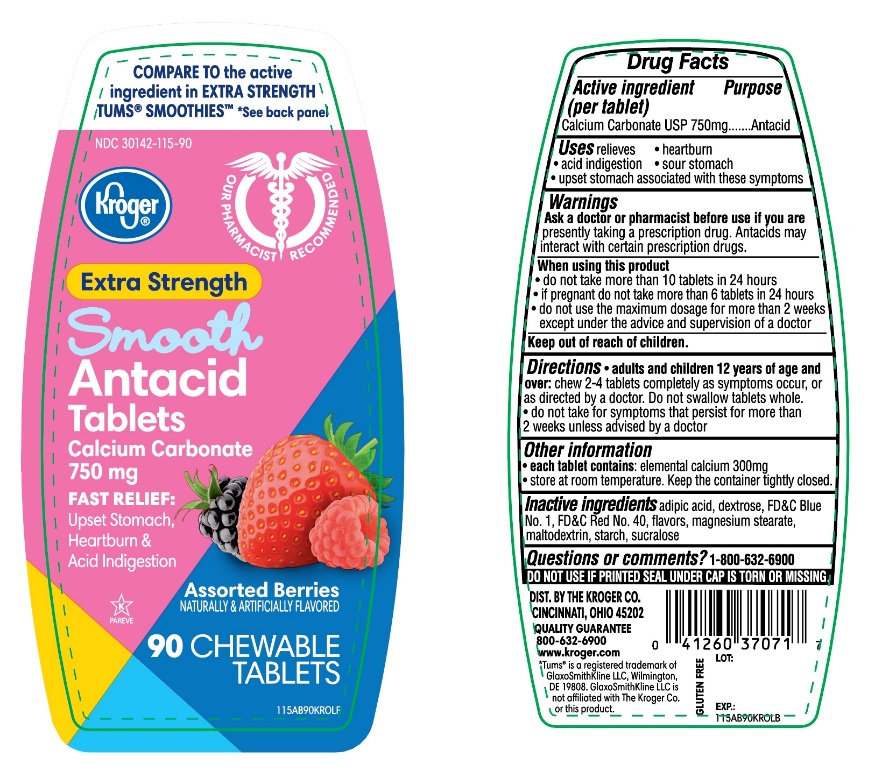 DRUG LABEL: Kroger Extra Strength Smooth Antacid

NDC: 30142-115 | Form: TABLET, CHEWABLE
Manufacturer: KROGER COMPANY
Category: otc | Type: HUMAN OTC DRUG LABEL
Date: 20250804

ACTIVE INGREDIENTS: CALCIUM CARBONATE 750 mg/1 1
INACTIVE INGREDIENTS: ADIPIC ACID; DEXTROSE, UNSPECIFIED FORM; FD&C BLUE NO. 1; FD&C RED NO. 40; MAGNESIUM STEARATE; MALTODEXTRIN; STARCH, CORN; SUCRALOSE

Kroger Smooth Antacid Assorted Berries 90 Chewable Tablets

Active ingredient (per tablet)

Calcium Carbonate USP 750mg

Purpose

Antacid

Uses

relieves

- heartburn
- acid indigestion
- sour stomach
- upset stomach associated with these symptoms

Warnings

Ask a doctor or pharmacist before use if you arepresently taking a prescription drug. Antacids may interact with certain prescription drugs.

When using this product

- do not take more than 10 tablets in 24 hours
- if pregnant do not take more than 6 tablets in 24 hours
- do not use the maximum dosage for more than 2 weeks except under the advice and supervision of a doctor

Directions

- adults and children 12 years of age and over:chew 2-4 tablets completely as symptoms occur or as directed by a doctor. Do not swallow tablets whole.
- do not take for symptoms that persist for more than 2 weeks unless advised by a doctor.

Other information

- each tablet contains:elemental calcium 300mg
- Store at room temperature. Keep the container tightly closed

Inactive ingredients

adipic acid, dextrose, FD&C Blue No. 1, FD&C Red No. 40, flavors, magnesium stearate, maltodextrin, starch, sucralose.

Questions?

1-800-632-6900

Safety sealed: DO NOT USE IF PRINTED SEAL UNDER CAP IS TORN OR MISSING

Package/Label Principal Display Panel

Kroger®

COMPARE TO active ingredient in EXTRA STRENGTH TUMS® SMOOTHIES™

*See back panel

NDC 30142-115-90

FAST RELIEF: Upset Stomach, Heartburn and Acid Indigestion

Extra Strength

Smooth Antacid Tablets

Calcium Carbonate, 750 mg

Assorted Berry Flavor

90 CHEWABLE TABLETS

GLUTEN- FREE

Our Pharmacists Recommend

QUALITY GUARANTEE

800-632-6900 www.kroger.com

DISTRIBUTED BY:

THE KROGER CO.

CINCINNATI, OHIO 45202

*TUMS® is registered trademark of GlaxoSmithKline LLC, Wilmington, DE 19808.

GlaxoSmithKline LLC is not affiliated with The Kroger Co. or this product.